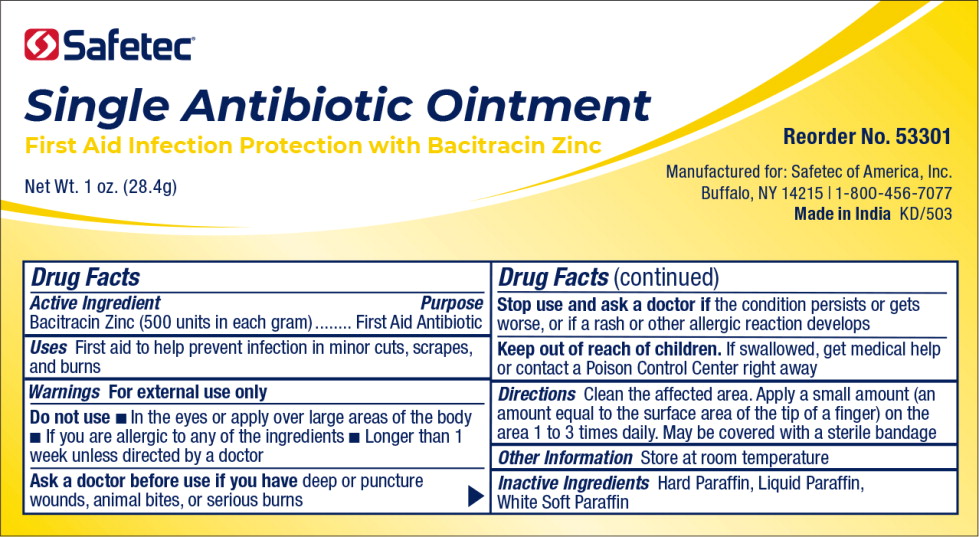 DRUG LABEL: Single Antibiotic
NDC: 61010-4404 | Form: OINTMENT
Manufacturer: Safetec of America, Inc.
Category: otc | Type: HUMAN OTC DRUG LABEL
Date: 20240214

ACTIVE INGREDIENTS: BACITRACIN ZINC 500 [iU]/1 g
INACTIVE INGREDIENTS: PARAFFIN; LIGHT MINERAL OIL; PETROLATUM

61010-4404 Triple Antibiotic with Pain Relief

Drug Facts

Active Ingredient

Bacitracin Zinc (500 units in each gram)

Purpose

First Aid Antibiotic

Uses

First aid to help prevent infection in minor cuts, scrapes, and burns

Warnings

For external use only

Do not use

■ In the eyes or apply over large areas of the body

■ If you are allergic to any of the ingredients

■ Longer than 1 week unless directed by a doctor

Ask a doctor before use if you havedeep or puncture wounds, animal bites, or serious burns

Stop use and ask a doctor ifthe condition persists or gets worse, or if a rash or other allergic reaction develops

Keep out of reach of children.If swallowed, get medical help or contact a Poison Control Center right away

Directions

Clean the affected area. Apply a small amount (an amount equal to the surface area of the tip of a finger) on the area 1 to 3 times daily. May be covered with a sterile bandage

Other Information

Store at room temperature

Inactive Ingredients

Hard Paraffin, Liquid Paraffin, White Soft Paraffin

Principal Display Panel – Tube Label

Safetec®

Single Antibiotic Ointment

First Aid Infection Protection with Bacitracin Zinc

Net Wt. 1 oz. (28.4g)

Reorder No. 53301

Manufactured for: Safetec of America, Inc.

Buffalo, NY 14215 | 1-800-456-7077

Made in IndiaKD/503